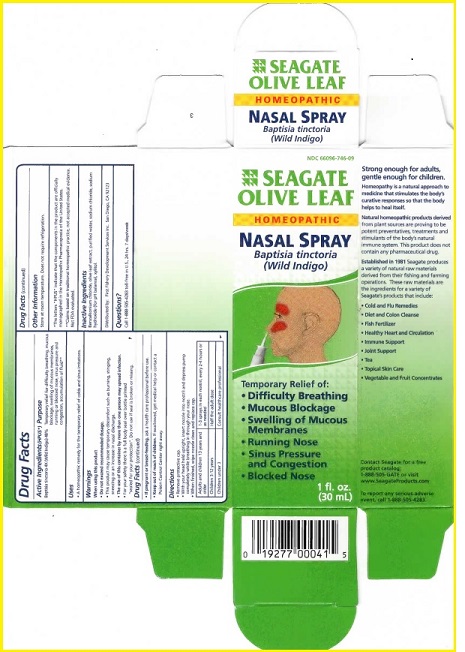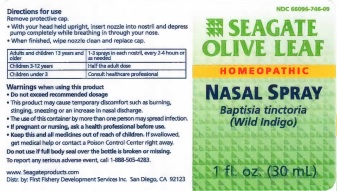 DRUG LABEL: Seagate Olive Leaf
NDC: 66096-746 | Form: SPRAY
Manufacturer: OHM PHARMA INC.
Category: homeopathic | Type: HUMAN PRESCRIPTION DRUG LABEL
Date: 20190129

ACTIVE INGREDIENTS: BAPTISIA TINCTORIA ROOT 4 [hp_X]/30 mL
INACTIVE INGREDIENTS: BENZALKONIUM CHLORIDE; OLEA EUROPAEA LEAF; WATER; SODIUM HYDROXIDE; SODIUM CHLORIDE; XYLITOL

Seagate Olive Leaf

ACTIVE INGREDIENT

Active Ingredients (HPUS*)*The letters "HPUS" indicate that the components in the product are officially monographed in the Homeopathic Pharmacopoeia of the United States

**Claims based on traditional homeopathic practice, not accepted medical evidence. Not FDA evaluated.

Uses

• A homeopathic remedy for the temporary relief of colds and sinus irrations.

Warnings

When using this product

• Do not exceed recommended dosage.

• This product may cause temporary discomfort such as burning, stinging,

sneezing or an increase in nasal discharge.

• The use of this container by more than one person may spread infection.

• For your safety there is a full body seal over bottle printed "sealed for your protection."

Do not use if seal is broken or missing.

•If pregnant or breast-feeding, ask a health care professional before use.

• Keep out of reach of children. If swallowed, get medical help or contact a Poison Control Center

right away.

Directions

• Remove protective cap.

• With your head held upright, insert nozzle into nostril and depress pump

completely while breathing in through your nose.

• When finished, wipe nozzle clean and replace cap.

Adults and children 13 years and older • 1-3 sprays in each nostril, every 2-4 hours or as needed.

Children 3-12 years • Half the adult dose.

Children under 3 • Consult healthcare professional

Other Information

Store at room temperature. Does not require refridgeration.

Inactive Ingredients

Benzalkonium chloride, olive leaf extract, purified water, sodium chloride, sodium hydroxide (for pH balance), xylitol.

Questions?

Call 1-888-505-4283 toll-free in U.S., 24 hrs 7 days/week

Contact Seagate for a free product catalog:

1-888-505-GATE or visit

www.SeagateProducts.com

To report any serious adverse event,

call 1-888-505-4283

PACKAGE LABEL

NDC: 66096-746-09

SEAGATE OLIVE LEAF

HOMEOPATHIC

NASAL SPRAY

Baptisia tinctoria

(Wild Indigo)

1 fl. oz (30 mL)

FRONT:

NDC: 66096-746-09

SEAGATE OLIVE LEAF

HOMEOPATHIC

NASAL SPRAY

Baptisia tinctoria

(Wild Indigo)

Temporary Relief of:

• Difficulty Breathing

• Mucous Blockage

• Swelling of Mucous

Membranes

• Running Nose

• Sinus Pressure

and Congestion

• Blocked Nose

RIGHT SIDE:

Strong enough for adults,

gentle enough for children.

Homeopathy is a natural approach to

medicine that stimulates the body's

curative responses so that the body helps to heal itself.

Natural homeopathic products derived

from plant sources are proving to be potent preservatives, treatments and

stimulants of the body's natural

immune system. This product does not

contain any pharmaceutical drug.

Established in 1981 Seagate produces

a variety of natural raw materials

derived from their fishing and farming

operations. These raw materials are

the ingredients for a variety of Seagate's products that include:

• Cold and Flu Remedies

• Diet and Colon Cleanse

• Fish Fertilizer

• Healthy Heart and Circulation

• Immune Support

• Tea

• Topical Skin Care

• Vegetable and Fruit Concentrates

1 fl. oz.

(30 mL)

Purpose

Temporary relief for difficulty breathing, mucous blockage, swelling or mucous membranes, running or blocked nose, sinus pressure and congestion, accumulation of fluid.**